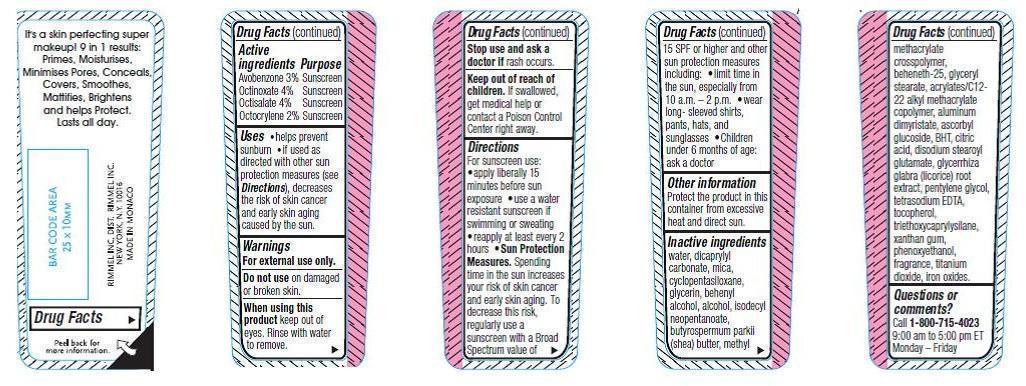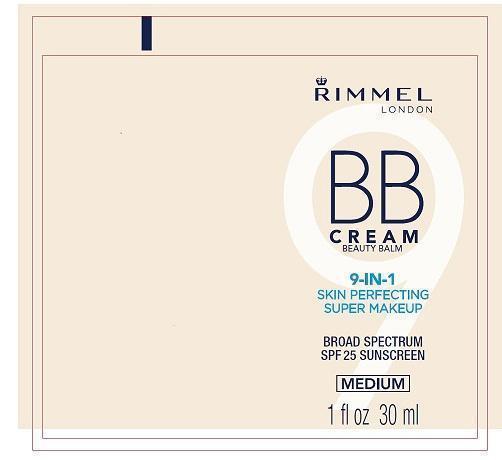 DRUG LABEL: Rimmel BB Beauty Balm
NDC: 76485-1025 | Form: LIQUID
Manufacturer: Rimmel Inc.
Category: otc | Type: HUMAN OTC DRUG LABEL
Date: 20121018

ACTIVE INGREDIENTS: Avobenzone 0.9 mL/30 mL; OCTINOXATE 1.2 mL/30 mL; OCTISALATE 1.2 mL/30 mL; OCTOCRYLENE 0.6 mL/30 mL
INACTIVE INGREDIENTS: Water; DICAPRYLYL CARBONATE; CYCLOMETHICONE 5; GLYCERIN; DOCOSANOL; ISODECYL NEOPENTANOATE; SHEA BUTTER; METHYL METHACRYLATE; BEHENETH-25; GLYCERYL STEARATE SE; CARBOMER COPOLYMER TYPE A (ALLYL PENTAERYTHRITOL CROSSLINKED); ALUMINUM DIMYRISTATE; ASCORBYL GLUCOSIDE; BUTYLATED HYDROXYTOLUENE; CITRIC ACID MONOHYDRATE; DISODIUM STEAROYL GLUTAMATE; GLYCYRRHIZA GLABRA; PENTYLENE GLYCOL; EDETATE SODIUM; TOCOPHEROL; TRIETHOXYCAPRYLYLSILANE; XANTHAN GUM; PHENOXYETHANOL; TITANIUM DIOXIDE; FERRIC OXIDE RED

Drug Facts

Drug Facts

Avobenzone 3%

Octinoxate 4%

Octisalate 4%

Octocrylene 2%

PURPOSE

Sunscreen

Keep out of reach of children. If swallowed, get medical help or contact a Poison Control Center right away.

INDICATIONS AND USAGE

- Helps prevent sunburn if used as directed with other sun protection measures (see Directions), decreases the risk of skin cancer and early skin aging caused by the sun.

WARNINGS

For external use only.

Do not use on damaged or broken skin.

When using this product keep out of eyes. Rinse with water to remove.

Stop use and ask a doctor if rash occurs.

DOSAGE AND ADMINISTRATION

For sunscreen use:

- apply liberally 15 minutes before sun exposure
- use a water resistant sunscreen if swimming or sweating
- reapply at least every 2 hours

Sun Protection Measures. Spending time in the sun increases your risk of skin cancer and early skin aging. To decrease this risk, regularly use a sunscreen with a Broad Spectrum value of 15 SPF or higher and other sun protection measures including:

- Limit tim in the sun, especially from 10 a.m-2p.m.
- Wear long-sleeved shirts, pants, hats, and sunglasses
- Children under 6 months of age: ask a doctor.

INACTIVE INGREDIENT

Aqua/Water/Eau, Dicaprylyl Carbonate, Mica, Cyclopentasiloxane, Glycerin, Behenyl Alcohol, Alcohol, Isodecyl Neopentanoate, Butyrospermum Parkii (Shea) Butter, Methyl Methacrylate Crosspolymer, Beheneth-25, Glyceryl Stearate, Acrylates/C12-22 Alkyl Methacrylate Copolymer, Aluminum Dimyristate, Ascorbyl Glucoside, BHT, Citric Acid, Disodium Stearoyl Glutamate, Clycyrrhiza Glabra (Licorice) Root Extract, Pentylene Glycol, Tetrasodium EDTA, Tocopherol, Triethoxycarpylylsilane, Xanthan Gum, Phenoxyethanol, Parfum/Fragrance, Titanium Dioxide (CI 77891), Iron Oxides (CI 77491, CI 77492, CI 77499)